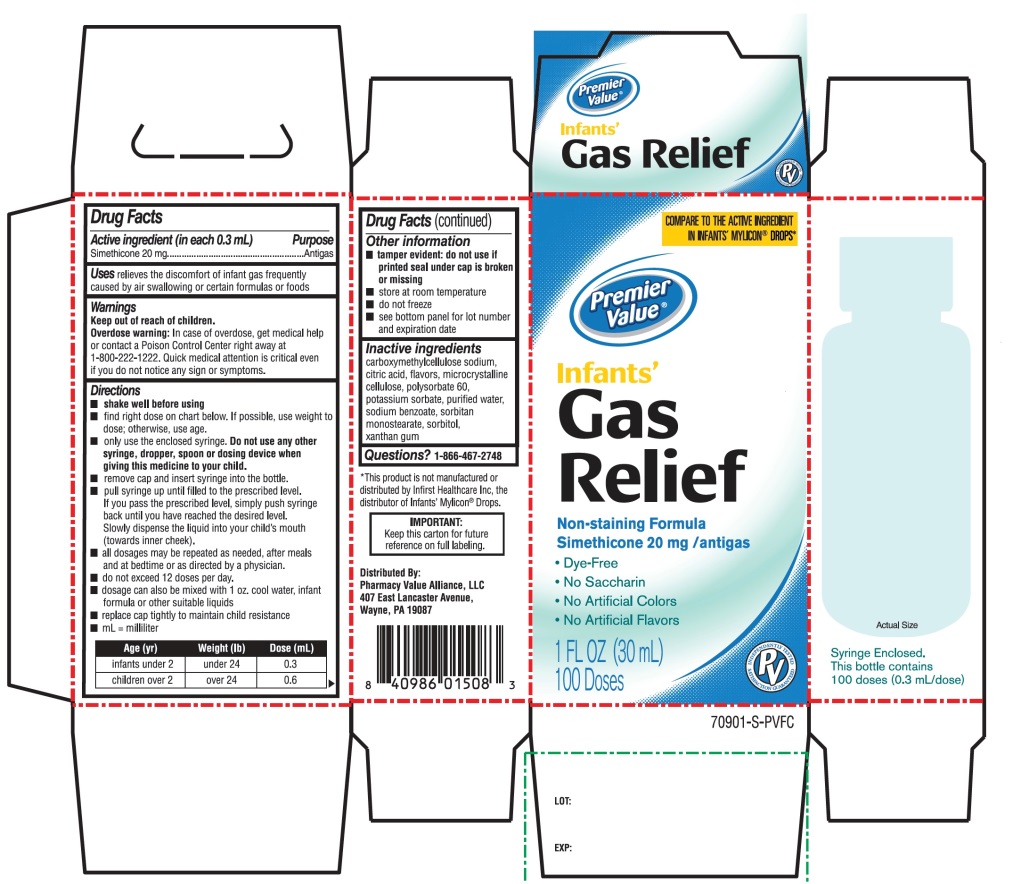 DRUG LABEL: premier value infants gas relief
NDC: 68016-670 | Form: EMULSION
Manufacturer: Chain Drug Consortium
Category: otc | Type: HUMAN OTC DRUG LABEL
Date: 20241028

ACTIVE INGREDIENTS: DIMETHICONE, UNSPECIFIED 20 mg/0.3 mL
INACTIVE INGREDIENTS: CARBOXYMETHYLCELLULOSE SODIUM, UNSPECIFIED; ANHYDROUS CITRIC ACID; MICROCRYSTALLINE CELLULOSE; POLYSORBATE 60; POTASSIUM SORBATE; WATER; SODIUM BENZOATE; SORBITAN MONOSTEARATE; SORBITOL; XANTHAN GUM

Premier Value Infants' Drops Gas Relief Drug Facts

Active ingredient (in each 0.3 mL)

Simethicone 20 mg

Purpose

Antigas

Uses

relieves the discomfort of infant gas frequently caused by air swallowing or certain formulas or foods

Directions

- shake well before using
- all dosages may be repeated as needed, after meals and at bedtime or as directed by a physician. Do not exceed 12 doses per day.
- fill enclosed dropper to recommended dosage level and dispense liquid slowly into baby’s mouth, toward the inner cheek
- dosage can also be mixed with 1 oz. cool water, infant formula or other suitable liquids
- clean dropper after each use - replace bottle with original cap

age (yr) | weight (lb) | dose
infants under 2 | under 24 | 0.3 mL
children over 2 | over 24 | 0.6 mL

Other information

- tamper evident: do not use if printed seal under cap is torn or missing
- store at room temperature
- do not freeze
- see bottom panel for lot and expiration date

Inactive ingredients

carboxymethylcellulose sodium, citric acid, flavors, microcrystalline cellulose, polysorbate 60, potassium sorbate, purified water, sodium benzoate, sorbitan monostearate, sorbitol, xanthan gum

Principal Display Panel

COMPARE TO ACTIVE INGREDIENT IN INFANTS' MYLICON® DROPS*

Premier Value®

Infants'

Gas Relief

Non-Staining formula

Simethicone 20 mg/Antigas

- Dye Free
- No Saccharin
- No Artificial Colors
- No Artificial flavors

Syringe Enclosed. This Bottle contains 100 doses (0.3 mL/dose)

1 Fl. OZ (30ml)

100 Doses

Distributed by

Pharmacy Value Alliance, LLC

407 East Lancaster Avenue,

Wayne, PA 19087

*This product is not manufactured or distributed by Infirst Healthcare Inc., the distributor of Infants’ Mylicon® Drops.

Premier Value Infants' Gas Relief